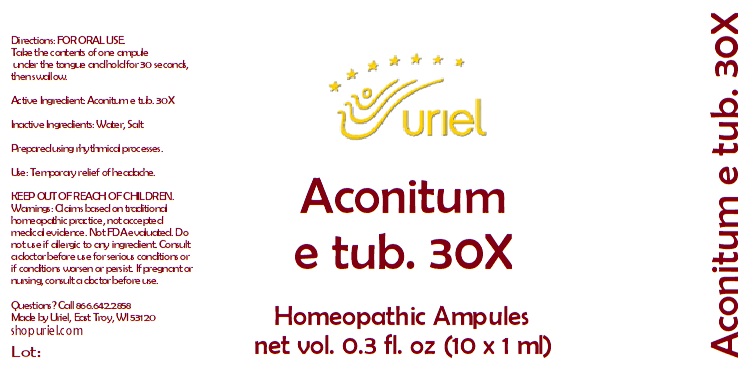 DRUG LABEL: Aconitum e tub. 30
NDC: 48951-1338 | Form: LIQUID
Manufacturer: Uriel Pharmacy Inc.
Category: homeopathic | Type: HUMAN OTC DRUG LABEL
Date: 20251106

ACTIVE INGREDIENTS: ACONITUM NAPELLUS 30 [hp_X]/1 mL
INACTIVE INGREDIENTS: WATER; SODIUM CHLORIDE

Aconitum e tub. 30

INDICATIONS AND USAGE

Directions: FOR ORAL USE.

DOSAGE AND ADMINISTRATION

Take the contents of one ampule under the tongue and hold for 30 seconds, then swallow.

Active Ingredient: Aconitum (Monkshood) 30X

Inactive Ingredients: Water, Salt

Prepared using rhythmical processes.

PURPOSE

Use: Temporary relief of headache

KEEP OUT OF REACH OF CHILDREN.

WARNINGS

Warnings: Claims based on traditional homeopathic practice, not accepted medical evidence. Not FDA evaluated. Do not use if allergic to any ingredient. Consult a doctor before use for serious conditions or if conditions worsen or persist. If pregnant or nursing, consult a doctor before use.

Questions? Call 866.642.2858
Made by Uriel, East Troy, WI 53120
shopuriel.com